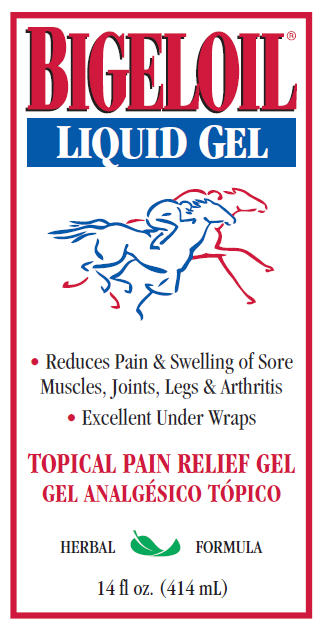 DRUG LABEL: Bigeloil
NDC: 11444-136 | Form: GEL
Manufacturer: W. F. Young, Inc.
Category: animal | Type: OTC ANIMAL DRUG LABEL
Date: 20241101

ACTIVE INGREDIENTS: MENTHOL, UNSPECIFIED FORM 2 g/112 mL

BIGELOIL®
LIQUID GEL

Can be used before, during and after competition

Can also be used on dogs

Indications

For temporary relief of minor pain and swelling from sprains, strains, bruises, arthritis, overworked muscles and minor wounds.

Directions for Use

Rub onto sore area 3 to 4 times a day. For faster relief, rub with hair and wrap or blanket. For minor cuts and scrapes apply without rubbing.

Caution: Avoid contact with eyes and mucous membranes.

Stop using if skin irritation develops or symptoms persist for more than 10 days.

For severe injuries consult a veterinarian.

For external use only. Keep out of reach of children.

Warning

Flammable. Keep away from fire, sparks and heated surfaces.

Store at room temperature.

For animal use only.

Active Ingredient

Menthol 2%. Also contains Alcohol: 60%.

Distributed by:
W. F. Young, Inc.
302 Benton Drive
E. Longmeadow, MA 01028 USA
© WFY
www.absorbine.com
RM 342360-5

PRINCIPAL DISPLAY PANEL - 414 mL Bottle Label

BIGELOIL®
LIQUID GEL

• Reduces Pain & Swelling of Sore
Muscles, Joints, Legs & Arthritis

• Excellent Under Wraps

TOPICAL PAIN RELIEF GEL

HERBAL FORMULA

14 fl oz. (414 mL)